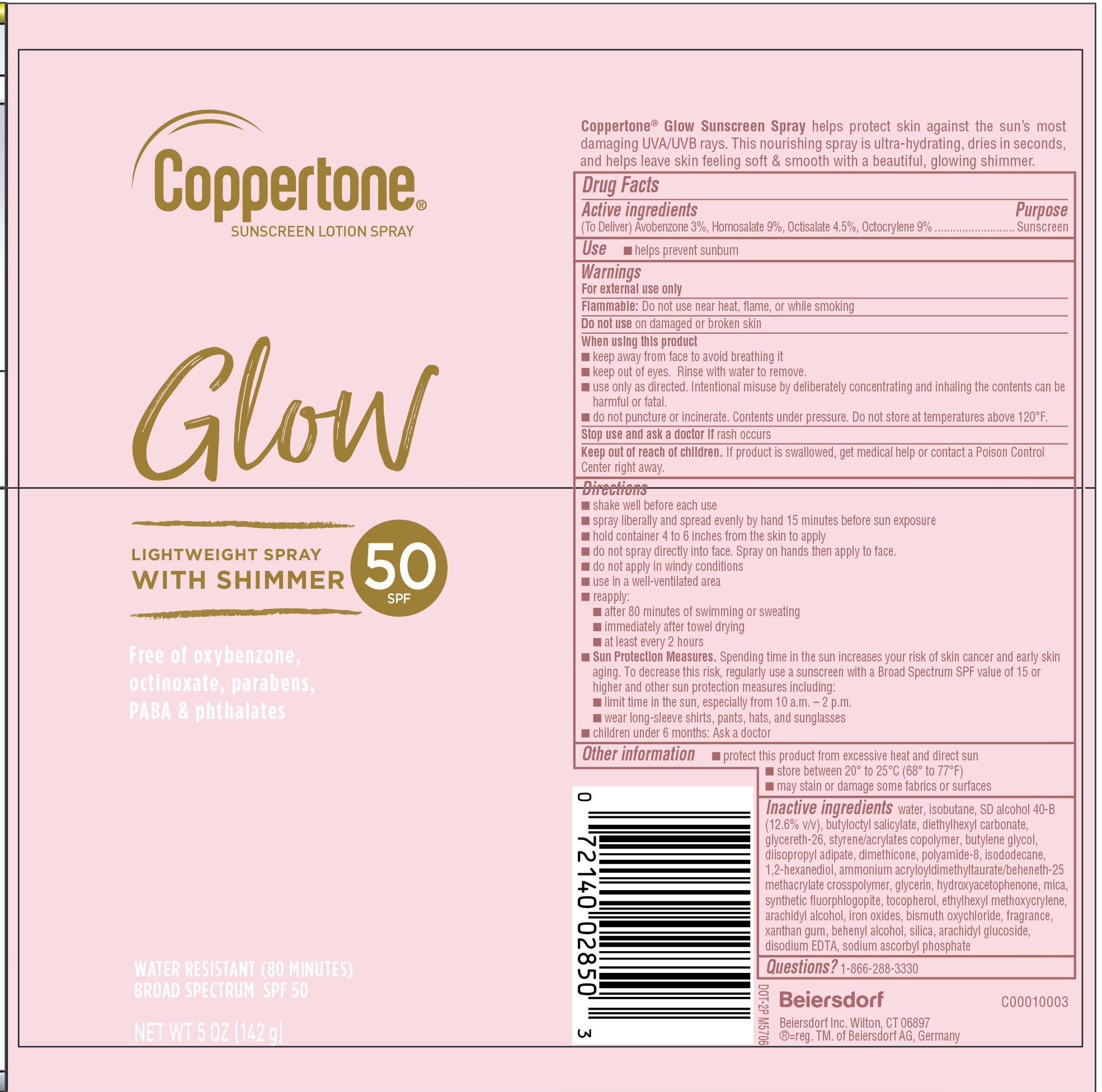 DRUG LABEL: Coppertone Glow Sunscreen SPF 50
NDC: 66800-0004 | Form: AEROSOL, SPRAY
Manufacturer: Beiersdorf Inc
Category: otc | Type: HUMAN OTC DRUG LABEL
Date: 20251231

ACTIVE INGREDIENTS: OCTOCRYLENE 90 mg/1 g; AVOBENZONE 30 mg/1 g; HOMOSALATE 90 mg/1 g; OCTISALATE 45 mg/1 g
INACTIVE INGREDIENTS: ALCOHOL; BISMUTH OXYCHLORIDE; ARACHIDYL ALCOHOL; DIISOPROPYL ADIPATE; ISODODECANE; 1,2-HEXANEDIOL; GLYCERIN; DIMETHICONE; WATER; BUTYLOCTYL SALICYLATE; DIETHYLHEXYL CARBONATE; COBALT DISODIUM EDETATE; SODIUM ASCORBYL PHOSPHATE; HYDROXYACETOPHENONE; ISOBUTANE; GLYCERETH-26; MAGNESIUM POTASSIUM ALUMINOSILICATE FLUORIDE; DOCOSANOL; ARACHIDYL GLUCOSIDE; TOCOPHEROL; ETHYLHEXYL METHOXYCRYLENE; FERRIC OXIDE YELLOW; FRAGRANCE FRESH CITRUS FLORAL ORC1501495; STYRENE/ACRYLAMIDE COPOLYMER (MW 500000); BUTYLENE GLYCOL; POLYAMIDE-8 (4500 MW); AMMONIUM ACRYLOYLDIMETHYLTAURATE/BEHENETH-25 METHACRYLATE CROSSPOLYMER (52000 MPA.S); MICA; SILICON DIOXIDE; XANTHAN GUM

Glow Spray Sunscreen SPF 50

Drug Facts

Active Ingredients

(To Deliver) Avobenzone 3%, Homosalate 9%, Octisalate 4.5%, Octocrylene 9%

Purpose

Sunscreen

Use

■ helps prevent sunburn

Warnings

For external use only

Flammable: Do not use near heat, flame, or while smoking

Do not use on damaged or broken skin

When using this product

■ keep away from face to avoid breathing it

■ keep out of eyes. Rinse with water to remove.

■ use only as directed. Intentional misuse by deliberately concentrating and inhaling the contents can be harmful or fatal.

■ do not puncture or incinerate. Contents under pressure. Do not store at temperatures above 120˚F.

Stop use and ask a doctor ifrash occurs

Keep out of reach of children.If product is swallowed, get medical help or contact a Poison Control Center right away.

Directions

■ shake well before each use

■ spray liberally and spread evenly by hand 15 minutes before sun exposure

■ hold container 4 to 6 inches from the skin to apply

■ do not spray directly into face. Spray on hands then apply to face.

■ do not apply in windy conditions

■ use in a well-ventilated area

■ reapply:

■ after 80 minutes of swimming or sweating

■ immediately after towel drying

■ at least every 2 hours

■ Sun Protection Measures.Spending time in the sun increases your risk of skin cancer and early skin aging. To decrease this risk, regularly use a sunscreen with a Broad Spectrum SPF value of 15 or higher and other sun protection measures including:

■ limit time in the sun, especially from 10 a.m. – 2 p.m.

■ wear long-sleeve shirts, pants, hats, and sunglasses

■ children under 6 months: Ask a doctor

Other Information

■ protect this product from excessive heat and direct sun

■ store between 20˚ to 25˚C (68˚ to 77˚F)

■ may stain or damage some fabrics or surfaces

Inactive Ingredients

water, isobutane, SD alcohol 40-B (12.6% v/v), butyloctyl salicylate, diethylhexyl carbonate, glycereth-26, styrene/acrylates copolymer, butylene glycol, diisopropyl adipate, dimethicone, polyamide-8, isododecane, 1,2-hexanediol, ammonium acryloyldimethyltaurate/beheneth-25 methacrylate crosspolymer, glycerin, hydroxyacetophenone, mica, synthetic fluorphlogopite, tocopherol, ethylhexyl methoxycrylene, arachidyl alcohol, iron oxides, bismuth oxychloride, fragrance, xanthan gum, behenyl alcohol, silica, arachidyl glucoside, disodium EDTA, sodium ascorbyl phosphate

Questions?

1-866-288-3330

PACKAGE LABEL

Coppertone Glow Sunscreen Lotion Spray

Glow

Lightweight Spray with Shimmer

SPF 50

Free of oxybenzone, octinoxate, parabens, PABA & phthlates

Water Resistant (80 minutes)

Broad Spectrum SPF 50

NET WT 5 OZ (142g)